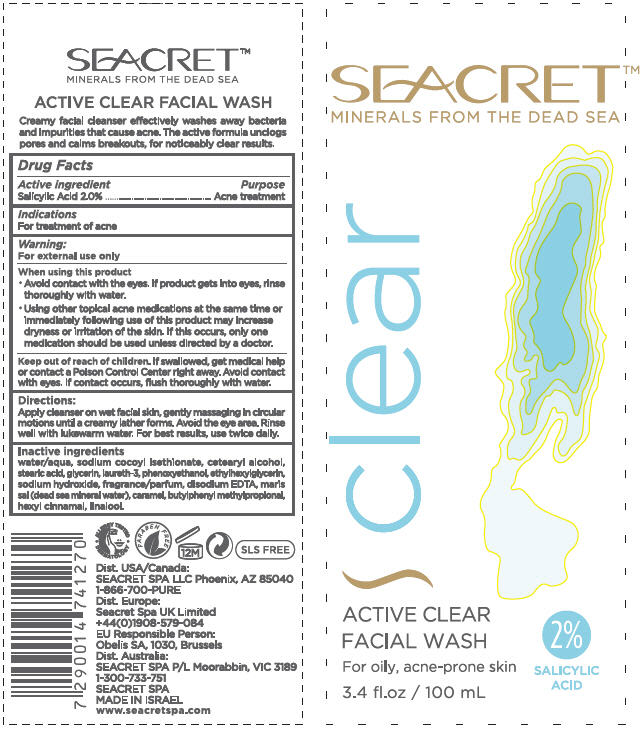 DRUG LABEL: Active Clear Facial Wash
NDC: 69915-001 | Form: LIQUID
Manufacturer: Seacret Spa LLC
Category: otc | Type: HUMAN OTC DRUG LABEL
Date: 20150624

ACTIVE INGREDIENTS: Salicylic Acid 20 mg/1 mL
INACTIVE INGREDIENTS: Water; Sodium Cocoyl Isethionate; Cetostearyl alcohol; Stearic Acid; Glycerin; Laureth-3; Phenoxyethanol; Ethylhexylglycerin; Sodium Hydroxide; Edetate Disodium; Caramel; Butylphenyl Methylpropional; .Alpha.-Hexylcinnamaldehyde; Linalool, (+/-)-

Active Clear Facial Wash

Drug Facts

Active ingredient

Salicylic Acid 2.0%

Purpose

Acne treatment

Indications

For treatment of acne

Warnings

For external use only

When using this product

- Avoid contact with the eyes. If product gets into eyes, rinse thoroughly with water.
- Using other topical acne medications at the same time or immediately following use of this product may increase dryness or irritation of the skin. If this occurs, only one medication should be used unless directed by a doctor.

Keep out of reach of children. If swallowed, get medical help or contact a Poison Control Center right away. Avoid contact with eyes. If contact occurs, flush thoroughly with water.

Directions

Apply cleanser on wet facial skin, gently massaging in circular motions until a creamy lather forms. Avoid the eye area. Rinse well with lukewarm water. For best results, use twice daily.

Inactive ingredients

water/aqua, sodium cocoyl isethionate, cetearyl alcohol, stearic acid, glycerin, laureth-3, phenoxyethanol, ethylhexylglycerin, sodium hydroxide, fragrance/parfum, disodium EDTA, maris sal (dead sea mineral water), caramel, butylphenyl methylpropional, hexyl cinnamal, linalool

PRINCIPAL DISPLAY PANEL - 100 mL Tube Label

SEACRET™
MINERALS FROM THE DEAD SEA

clear

ACTIVE CLEAR
FACIAL WASH
For oily, acne-prone skin

2%
SALICYLIC
ACID

3.4 fl.oz / 100 mL